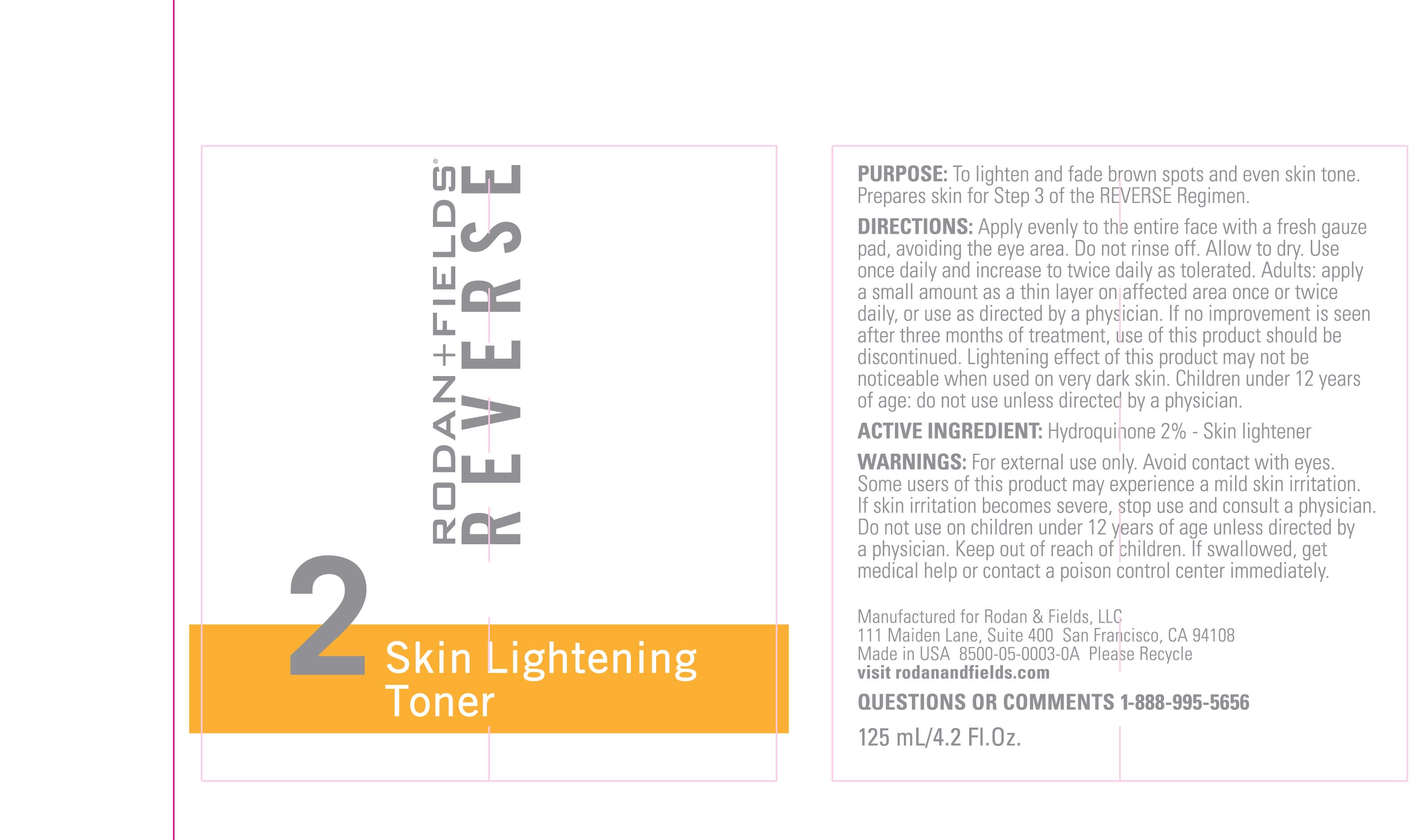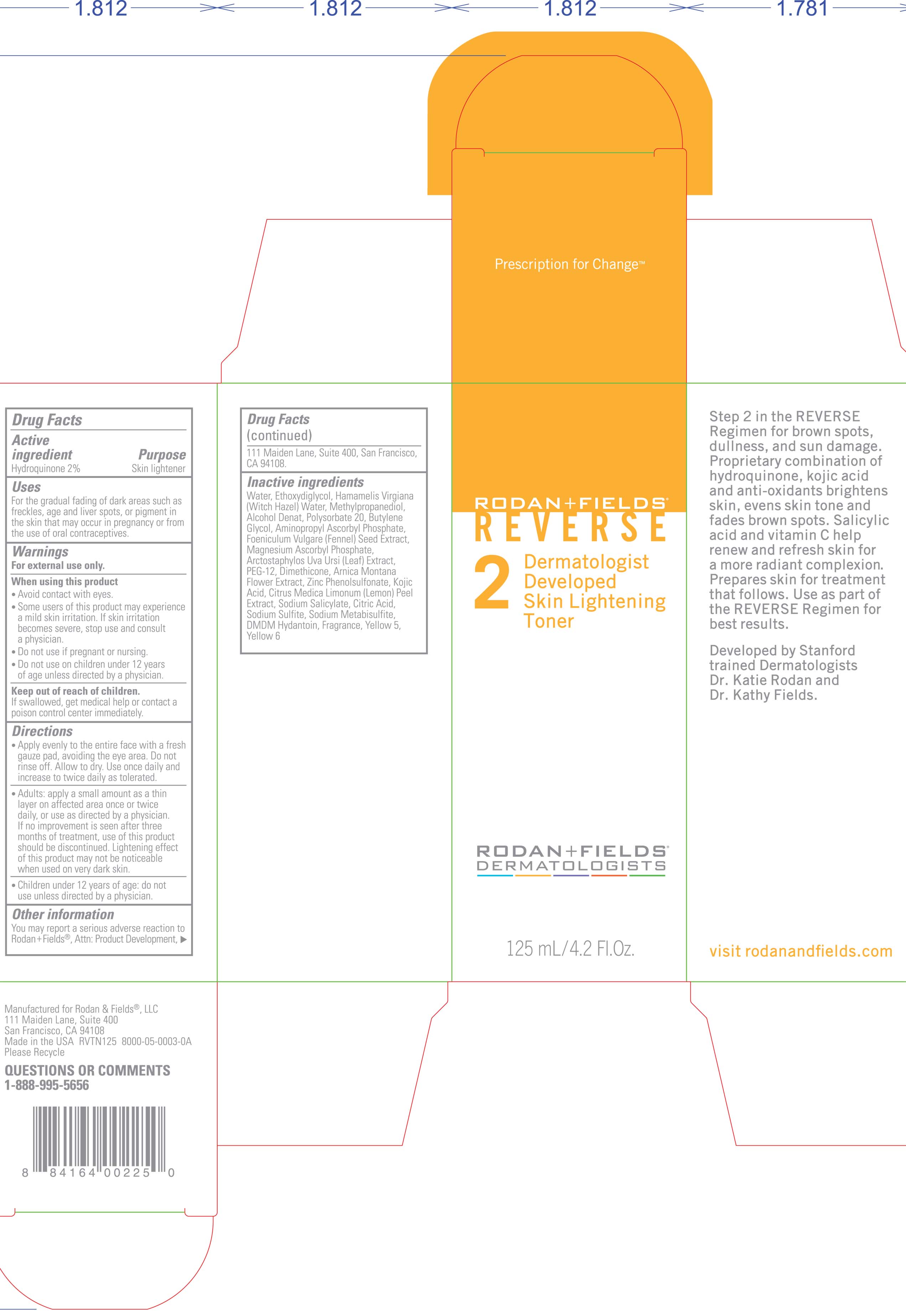 DRUG LABEL: Skin Lightening
NDC: 14222-1615 | Form: LIQUID
Manufacturer: Rodan & Fields, LLC.
Category: otc | Type: HUMAN OTC DRUG LABEL
Date: 20120124

ACTIVE INGREDIENTS: HYDROQUINONE 2 mL/100 mL
INACTIVE INGREDIENTS: DIETHYLENE GLYCOL MONOETHYL ETHER; WITCH HAZEL; METHYLPROPANEDIOL; POLYSORBATE 20; BUTYLENE GLYCOL; FENNEL SEED; MAGNESIUM ASCORBYL PHOSPHATE; ARCTOSTAPHYLOS UVA-URSI LEAF; POLYETHYLENE GLYCOL 600; DIMETHICONE; ARNICA MONTANA FLOWER; ZINC PHENOLSULFONATE; KOJIC ACID; LEMON PEEL; SODIUM SALICYLATE; SODIUM SULFITE; SODIUM METABISULFITE; DMDM HYDANTOIN; FD&C YELLOW NO. 5; FD&C YELLOW NO. 6

Rodan and Fields Reverse 2 Skin Toner

ACTIVE INGREDIENT

Hydroquinone 2%

PURPOSE

Skin Lightening

Keep out of reach of children

if swallowed, get medical help or contact a poison control center immediately.

WARNINGS

avoid contact with eyes.

some user of this product may experience a mild skin irritation. if skin irritation becomes severe , stop use and consult a physician.

do not use if pregnant or nursing.

do not use on children under 12 years of age unless directed by a physician.

DOSAGE AND ADMINISTRATION

apply evenly to the entire face with a fresh gauze pad, avoiding the eye area. do not rinse off, allow to dry. use once daily and increase to twice daily as tolerated.
Adult: apply a small amount as a think layer in affected area once or twice daily, or use as directed by a physician . if no improvement is seen after three months of treatment, use of this product should be discontinued . lightening effect of this product may not be noticeable when used on very dark skin.
children under 12 years of age: do not use unless directed by a physician.

INACTIVE INGREDIENT

Water (aqua), Ethoxydiglycol, Hamamelis Virgiana (Witch Hazel) Water, Methylpropanediol, Alcohol Denat, Polysorbate 20, Butylene Glycol, Aminopropyl Ascorbyl Phosphate, Foeniculum Vulgare (Fennel) Seed Extract, Magnesium Ascorbyl Phosphate, Arctostaphylos Uva Ursi (leaf) Extract, PEG-12, Dimethicone, Arnica Montana Flower Extract, Zinc Phenolsulfonate, Kojic Acid, Citrus Medica Limonum (Lemon) Peel Extract, Sodium Salicylate, Citric Acid, Sodium Sulfite, Sodium Metabisulfite, DMDM Hydantoin, Fragrance, Yellow 5, Yellow 6

INDICATIONS AND USAGE

for external use only

PACKAGE LABEL

Rodan and Fields

Reverse

Dermatologist developed skin lightening toner

125 mL/ 4.2 Fl. Oz.